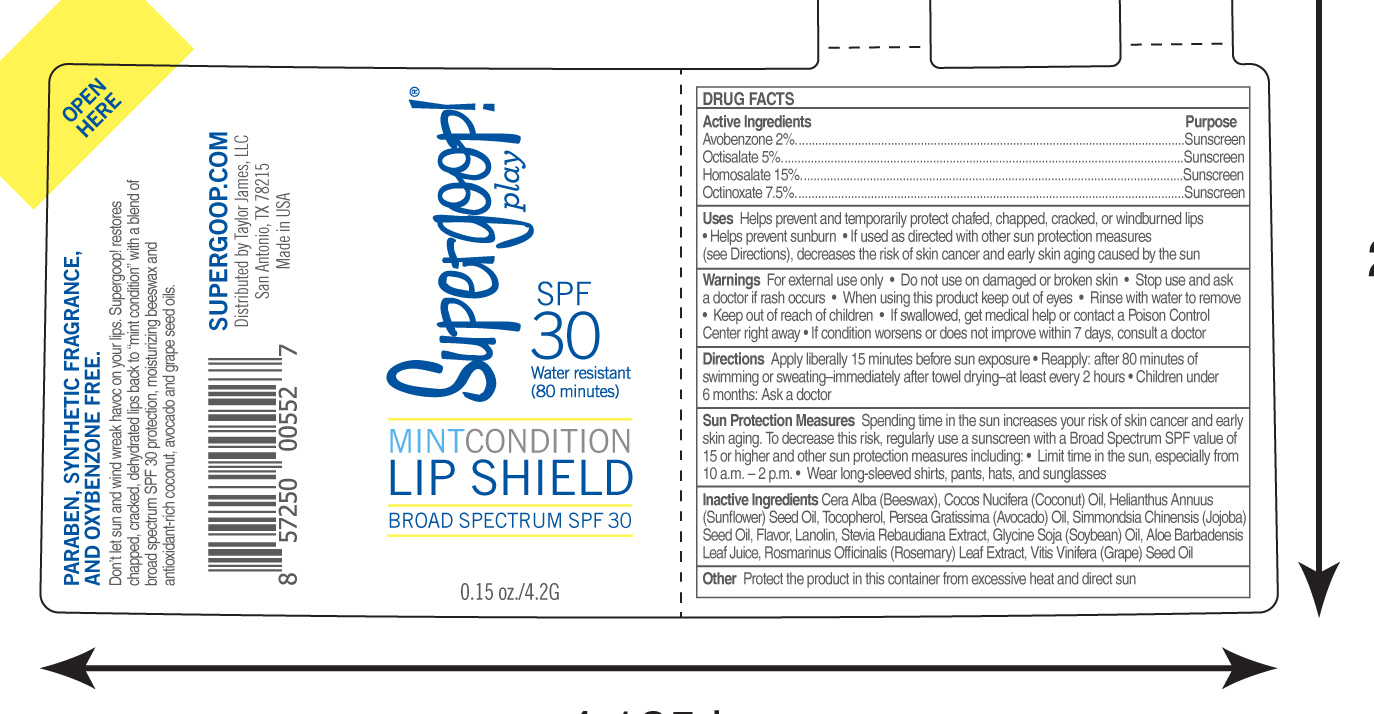 DRUG LABEL: Mint Condition Lip Shield SPF 30
NDC: 75936-201 | Form: STICK
Manufacturer: T AYLO R JAMES, LT D.
Category: otc | Type: HUMAN OTC DRUG LABEL
Date: 20170117

ACTIVE INGREDIENTS: AVOBENZONE 2 g/100 g; OCTISALATE 5 g/100 g; HOMOSALATE 15 g/100 g; OCTINOXATE 7.5 g/100 g
INACTIVE INGREDIENTS: WHITE WAX; COCONUT OIL; SUNFLOWER OIL; TOCOPHEROL; AVOCADO OIL; JOJOBA OIL; LANOLIN; STEVIA REBAUDIUNA LEAF; SOYBEAN OIL; ALOE VERA LEAF; ROSEMARY; GRAPE SEED OIL

Mint Condition Lip Shield Broad Spectrum SPF 30

Active Ingredients Purpose
Avobenzone 2% ....................... Sunscreen

Octisalate 5% ........................... Sunscreen

Homosalate 15% ..................... Sunscreen

Octinoxate 7.5% ...................... Sunscreen

PURPOSE

Uses Helps prevent and temporarily protect chafed, chapped, cracked, or windburned lips

- Helps preven sunburns
- If used as directed with other sun protection measures (see Directions), decreases the risk of skin cancer and early skin aging caused by the sun

Keep out of reach of children

Stop use and ask a doctor if rash occurs

Warnings For external use only

- Do not use on damaged or broken skin
- when using this product keep out of eyes
- Rinse with water to remove
- If swallowed, get medical help or contact a Poison Control Center right away
- If condition worsens or does not improve within 7 days, consult a doctor

DOSAGE AND ADMINISTRATION

Directions Apply liberally 15 minutes before sun exposure

- Reapply: after 80 minutes of swimming or sweating-immediately after towel drying-at least every 2 hours
- Children under 6 months: Ask a doctor

Sun Protection Measures: Spening time in the sun increases your risk of skin cancer and early skin aging. To decrease this risk, regularly use a sunscreen with a Broad Spectrum SPF value of 15 or higher and other sun protection measures including:

- Limit time in the sun, especially from 10a.m. - 2p.m.
- Wear long-sleeved shirts, pants, hats, and sunglasses

INACTIVE INGREDIENT

Cera Alba (Beeswax), Cocos Nucifera (Coconut) Oil, Helianthus Annuus (Sunflower) Seed Oil, Tocopherol, Persea Gratissima (Avocado) OIl, Simmondsia Chenensis (Jojoba) Seed Oil, Flavor, Lanolin, Stevia Rebaudiana Extract, Glycine Soja (Soybean) Oil, Aloe Barbadensis Leaf Juice, Rosmarinus Officinalis (Rosmary) Leaf Extract, Vitis Vinifera (Grape) Seed Oil

PACKAGE LABEL

Mint Condition Lip Shield

Broad Spectrum SPF 30

0.15oz./4.2G